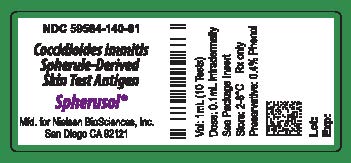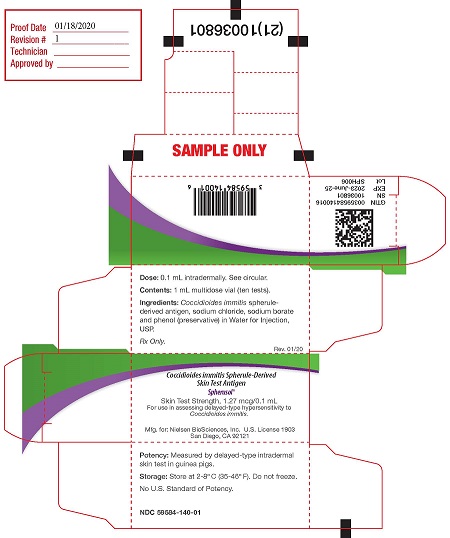 DRUG LABEL: Spherusol
NDC: 59584-140 | Form: INJECTION, SOLUTION
Manufacturer: Nielsen BioSciences, Inc.
Category: prescription | Type: HUMAN PRESCRIPTION DRUG LABEL
Date: 20250114

ACTIVE INGREDIENTS: COCCIDIOIDES IMMITIS SPHERULE 12.7 ug/1 mL
INACTIVE INGREDIENTS: SODIUM CHLORIDE .009 g/1 mL; SODIUM BORATE .00014 g/1 mL; PHENOL .0045 mL/1 mL; WATER .99 mL/1 mL

HIGHLIGHTS OF PRESCRIBING INFORMATION

These highlights do not include all the information needed to use Spherusol® safely and effectively. See full prescribing information for Spherusol®.
Coccidioides immitis Spherule-Derived Skin Test Antigen-
Spherusol®
Solution for Intradermal Injection
Initial U.S. Approval: July 2011
Nielsen BioSciences, Inc. U.S. Lic. No. 1903
Mfd. by Allermed Laboratories, Inc. U.S. Lic. No. 0467

WARNING

See full prescribing information for complete boxed warning

- The expected response to Spherusol® is a local area of inflammation at the site of the skin test. The reaction is usually dime to quarter size reaching maximum diameter between 24 and 48 hours. Larger accelerated reactions can occur, which may require treatment with local cold compresses and anti-inflammatory medication. (2.3, 6.1)
- Systemic reactions can occur with skin test antigens and in certain individuals these reactions may be life-threatening or cause death. Emergency measures and personnel trained in their use should be immediately available. Patients should be observed for at least 20 minutes following the administration of a skin test. (5.3, 6.2)
- Spherusol® should never be given intravenously. (5)
- To report SUSPECTED ADVERSE REACTIONS, contact Nielsen BioSciences, Inc. at (855) 855-1212 or MEDWATCH, Food and Drug Administration (FDA), 5600 Fishers Lane, Rockville, MD 20852-9782. Telephone: (800) 332-1088 or www.vaers.hhs.gov. (6.2)

1 INDICATIONS AND USAGE

- Spherusol® is a skin test antigen indicated for the detection of delayed-type hypersensitivity to Coccidioides immitis in individuals with a history of pulmonary coccidioidomycosis. Spherusol® is approved for use in individuals 18-64 years of age.
- The use of Spherusol® to detect delayed-type hypersensitivity responses in a general population with unknown exposure to C. immitis has not been evaluated.
- Persons with acute or disseminated coccidioidomycosis may not develop a delayed-type hypersensitivity response to Spherusol®.
- Persons with immunodeficiency and a history of coccidioidomycosis may not develop a delayed-type hypersensitivity response to Spherusol®.(1)

2 DOSAGE AND ADMINISTRATION

- A single 0.1 mL intradermal injection. Induration at injection site to be evaluated 48 hours after administration. (2.1, 2.3)

3 DOSAGE FORMS AND STRENGTHS

- Multi-dose vial (1 mL) containing a solution of spherule-derived C. immitis antigen, 1.27 mcg per 0.1mL. (3)

4 CONTRAINDICATIONS

- Severe allergic reaction (e.g., anaphylaxis) to Spherusol®, or any component of Spherusol® or other coccidioidin products. (4)

5 WARNINGS AND PRECAUTIONS

- Acute hypersensitivity reactions and anaphylaxis have occurred following the administration of other skin test antigens and may occur in individuals following the administration of Spherusol®. (5.1)
- Patients receiving beta-blocking drugs may be refractive to the usual dose of epinephrine in cases of hypersensitivity. (5.2)
- Any condition or agent that impairs or attenuates delayed type hypersensitivity reactions, including infections and use of immunosuppressive drugs, can potentially cause a false negative reaction to Spherusol®. (5.3)

6 ADVERSE REACTIONS

- The most commonly reported local adverse reactions were itching and swelling (>75%) and pain (>15%) within 7 days of administration.(6.1)
- To report SUSPECTED ADVERSE REACTIONS, contact Nielsen Biosciences, Inc. at (855) 855-1212 or Food and Drug Administration (FDA) at 1-800-332-1088 or www.vaers.hhs.gov. (6.3)

7 DRUG INTERACTIONS

- Corticosteroids and immunosuppressive agents may suppress the response to the skin test.(7.1)

8 USE IN SPECIFIC POPULATIONS

- The safety and effectiveness of Spherusol® in pregnant and nursing women have not been established. (8.1, 8.3)

FULL PRESCRIBING INFORMATION

WARNING

- The expected response to Spherusol® is a local area of inflammation at the site of the skin test. The reaction is usually dime to quarter size reaching maximum diameter between 24 and 48 hours. Larger accelerated reactions can occur, which may require treatment with local cold compresses and anti-inflammatory medication. (2.3, 6.1)
- Systemic reactions can occur with skin test antigens and in certain individuals these reactions may be life-threatening or cause death. Emergency measures and personnel trained in their use should be immediately available. Patients should be observed for at least 20 minutes following the administration of a skin test. (6.2)
- Spherusol® should never be given intravenously. (5)
- To report SUSPECTED ADVERSE REACTIONS, contact Nielsen BioSciences, Inc. at (855) 855-1212 or MEDWATCH, Food and Drug Administration (FDA), 5600 Fishers Lane, Rockville, MD 20852-9782. Telephone: (800) 332-1088 or www.vaers.hhs.gov. (6.2)

1 INDICATIONS AND USAGE

Spherusol® is a skin test antigen indicated for the detection of delayed-type hypersensitivity to Coccidioides immitis in individuals with a history of pulmonary coccidioidomycosis. Spherusol® is approved for use in individuals 18-64 years of age.

- The use of Spherusol® to detect delayed-type hypersensitivity responses in a general population with unknown exposure to C. immitis has not been evaluated.
- Persons with acute or disseminated coccidioidomycosis may not develop a delayed-type hypersensitivity response to Spherusol®.
- Persons with immunodeficiency and a history of coccidioidomycosis may not develop a delayed-type hypersensitivity response to Spherusol®.

2 DOSAGE AND ADMINISTRATION

2.1 Preparation for Administration

Spherusol® is a clear, colorless sterile solution for intradermal administration.

Parenteral drug products should be inspected visually for particulate matter and discoloration prior to administration, whenever solution and container permit. If any of these conditions exists, the skin test antigen should not be administered.

2.2 Administration:

Spherusol® is administered as a 0.1 mL dose by intradermal injection to the volar surface of the forearm using a tuberculin syringe (0.5 or 1.0 mL) and a ½ inch 26-27 gauge needle. The needle should be inserted bevel side up in the skin at a 15-20 degree angle. Intradermal injection of 0.1 mL Spherusol® will result in a bleb 5-10 mm in diameter at the injection site.

2.3 Skin Test Assessment

The injection site should be assessed for induration at 48 hours (±4 hours) following administration. The response to the skin test should be measured by taking the mean of the orthogonal diameters of the area of induration. A mean induration of ≥ 5 mm is considered a positive delayed-type hypersensitivity response to Spherusol®.

Repeat administration of Spherusol® has not been evaluated.

3 DOSAGE FORMS AND STRENGTHS

Spherusol® is a solution for intradermal injection supplied in a 1 mL multi-dose vial. Each 0.1 mL dose contains 1.27 mcg of spherule-derived Coccidioides immitis antigen.

4 CONTRAINDICATIONS

A severe allergic reaction (e.g., anaphylaxis) to Spherusol®, or any component of Spherusol® or other coccidioidin products is a contraindication to administration.

5 WARNINGS AND PRECAUTIONS

5.1 Prevention and Management of Acute Hypersensitivity Reactions

Prior to administration, the healthcare provider should review the medical history for possible skin test sensitivity and previous skin test related adverse reactions to assess the risks and benefits. Immediate hypersensitivity, to include severe systemic reactions, may occur following administration of skin test antigens. Medications and equipment to manage possible anaphylactic reactions should be available for immediate use. Patients should be observed for a minimum of 30 minutes following administration to assess for adverse reactions.

5.2 Patients on Beta Blockers

Patients receiving beta blockers may be unresponsive to the usual doses of epinephrine used to treat serious systemic reactions, including anaphylaxis.

5.3 Immunosuppression

Any condition or agent that impairs or attenuates delayed-type hypersensitivity reactions, including infections and use of immunosuppressive drugs, can potentially cause a false negative reaction to Spherusol®. [see Drug Interactions (7.1)]

6 ADVERSE REACTIONS

6.1 Clinical Trials Experience

Because clinical trials are conducted under widely varying conditions, adverse reaction rates observed in the clinical trials of a skin test antigen cannot be directly compared to rates in the clinical trials of another skin test antigen, and may not reflect the rates observed in practice. As with any skin test antigen, there is the possibility that broad use of Spherusol® could reveal adverse reactions not observed in clinical trials.

In a double-blinded placebo-controlled clinical trial conducted in areas of the U.S. endemic for C. immitis (Bakersfield, CA and Tucson, AZ), 54 adults (23-64 years of age) with a history of pulmonary coccidioidomycosis of at least 45 days duration, diagnosed by clinical findings, radiography and serological and/or mycological evidence of the disease, received a single dose of Spherusol® concomitantly with two licensed skin test extracts (Candin® and Trichophyton) and two controls (product diluent [thimerosal ≤0.0001%] and saline). Each intradermal injection of 0.1 mL of reagent was given at pre-determined sites on the right and left forearms. Solicited local adverse reactions and systemic adverse events occurring within 7 days after injection were recorded by study subjects via diary card. These events were also recorded on case report forms (CRFs) by study personnel during clinical visits 48 hours and 7 days following injections. Diary cards and CRFs did not record solicited local reactions by specific site. Local adverse reactions and systemic adverse events that occurred within 7 days were monitored until resolution. Reports of unsolicited adverse events and serious adverse events that occurred within 7 days after administration were collected on the diary cards or reported at study visits.

Table 1 lists the percentage of subjects reporting solicited local reactions (at any site) and solicited systemic adverse events within 7 days following the administration of Spherusol®, Candin®, Trichophyton, diluent control and placebo control.

Table 1. Frequency of Solicited Local Reactions and Systemic Adverse Events within 7 days of Administration of Spherusol®, Candin®, Trichophyton, Diluent Control and Saline Control in Subjects with a History of Pulmonary Coccidioidomycosis (N=53)
Symptom | Frequency (%)
Local ∗ | Any | Mild | Moderate | Severe
Itching | 85 | 36 | 47 | 2
Swelling | 79 | 36 | 41 | 2
Pain | 17 | 13 | 4 | 0
Necrosis/Ulceration | 4 | 2 | 0 | 2
Systemic
Increased heart rate | 4 | 2 | 2 | 0
Weakness | 6 | 2 | 4 | 0
Faintness | 0 | 0 | 0 | 0
Dizziness | 2 | 2 | 0 | 0
Nausea/cramps | 2 | 2 | 0 | 0
Flu-like symptoms | 7 | 2 | 6 | 0
Difficulty breathing/shortness of breath | 0 | 0 | 0 | 0
Any = Percentage of subjects experiencing adverse event of any intensity; Mild = Barely noticeable, not bothersome; Moderate = Distinctly noticeable discomfort; Severe = Needs medical attention. ∗ Local reactions occurring at any injection site

Of subjects with severe reactions, one subject required treatment with oral corticosteroids for ulceration and swelling. Based on investigator's determination the reaction was at the site of Trichophyton injection. All severe reactions resolved without sequelae.

During the 7 days following administration two subjects reported unsolicited adverse events: one subject reported joint pain, fatigue, cough, sensitivity at a test site (test site not specified), and one subject with erythema immediately after administration (test site not specified). The intensities of these unsolicited adverse events were not recorded.

No serious adverse events or deaths were reported during the clinical study.

6.2 To report SUSPECTED ADVERSE REACTIONS, contact Nielsen BioSciences, Inc. at (855) 855-1212 or MEDWATCH, Food and Drug Administration (FDA), 5600 Fishers Lane, Rockville, MD 20852-9782. Telephone: (800) 332-1088 or www.vaers.hhs.gov.

7 DRUG INTERACTIONS

7.1 Corticosteroids and Immunosuppressives

Corticosteroids and Immunosuppressive agents may suppress the response to the skin test. Pharmacologic doses of corticosteroids may suppress the response to skin test antigens after two weeks of therapy. The mechanism of suppression is thought to involve a decrease in monocytes and lymphocytes, particularly T-cells. The normal DTH response usually returns to pre-treatment levels within several weeks after steroid therapy is discontinued.(5) The use of Spherusol® has not been evaluated during or following the use of corticosteroids or immunosuppressive agents.

7.2 Antifungal Medications

It is not known if concurrent treatment with antifungal medications interferes with delayed-type hypersensitivity responses to Spherusol® in patients with a history of pulmonary coccidioidomycosis.

8 USE IN SPECIFIC POPULATIONS

8.1 Pregnancy

The safety and effectiveness of Spherusol® in pregnant women have not been established.

Pregnancy Category C

Animal reproduction studies have not been conducted with Spherusol®. It is also not known whether Spherusol® can cause fetal harm when administered to a pregnant woman or affect reproduction capacity. Spherusol® should be given to a pregnant woman only if clearly needed.

8.2 Labor and Delivery

No information is available to assess the effects of Spherusol® on childbirth.

8.3 Nursing Mothers

The safety and effectiveness of Spherusol® in nursing women have not been established.

It is not known whether Spherusol® is excreted in human milk. However, because the potential exists for Spherusol® to be excreted in human milk, caution should be exercised when administering Spherusol® to a nursing woman.

8.4 Pediatric Use

The safety and effectiveness of Spherusol® in the pediatric population have not been established.

8.5 Geriatric Use

The safety and effectiveness of Spherusol® have not been established in individuals >65 years of age.

11 DESCRIPTION

Spherusol® is a sterile aqueous solution of extracts of C. immitis spherules. The multi-dose vial contains 0.9% sodium chloride and 0.014% sodium borate with 0.4% phenol as a preservative. Residual thimerosal from the manufacturing process is present at a concentration of ≤0.0001% (<0.05 mcg mercury/0.1 mL dose). Each 0.1 mL dose contains 1.27 mcg of spherule-derived antigen.

The potency of each lot of Spherusol® is determined in sensitized guinea pigs.

12 CLINICAL PHARMACOLOGY

12.1 Mechanism of Action

In individuals with a history of pulmonary coccidioidomycosis Spherusol® is thought to elicit a cellular immune reaction to C. immitis, as evidenced by a delayed-type hypersensitivity (DTH) response to Coccidioidin(1,2,3,4). The general mechanism of the DTH response is based on the interaction of antigen with CD4 and CD8 lymphocytes followed by the secretion of interleukins and other lymphokines from macrophage cells. The release of effector molecules causes endothelial cells lining the blood vessels to become permeable and allows fibrinogen to escape into the surrounding tissue where it is converted to fibrin. The deposition of fibrin and the accumulation of T-cells and monocytes within the extracellular spaces cause the tissue to swell and become indurated. This process is usually detectable in 18 hours and peaks at 48 hours.(5)

14 CLINICAL STUDIES

The delayed-type hypersensitivity response following administration of Spherusol® was evaluated in one U.S. study which enrolled persons with a history of coccidioidomycosis. Two further U.S. studies enrolled subjects without a history of coccidioidomycosis; in one of these studies subjects had a history of histoplasmosis. In each study, concomitant with Spherusol®, two additional skin test extracts, Candin® and Trichophyton (positive controls), were administered along with a saline (negative control) and a diluent containing ≤ 0.0001% thimerosal (negative control). All skin tests and controls were administered as 0.1 mL doses in a randomized pattern on the volar surface of the forearms. Investigators and subjects were blinded to identity and placement of skin test antigens and controls. Responses were read at 48 hours (±4 hours) following administration. Induration responses were measured for each test site and recorded as the mean of the orthogonal diameters. A positive skin test was defined as a mean induration of ≥ 5 mm at 48 hours following administration of the antigens or controls. For each subject Spherusol® skin test results were considered valid if ≥ 5 mm was observed at the positive control antigen sites and no induration ≥ 5 mm was observed at the negative control sites.

The use of Spherusol® to detect delayed-type hypersensitivity response in a general population with unknown exposure to C. immitis has not been evaluated.

14.1 Induration Response in Subjects With a History of Pulmonary Coccidioidomycosis

A multicenter, double-blinded study in endemic areas (Bakersfield, CA and Tucson, AZ) enrolled 54 adults with a history of pulmonary coccidioidomycosis diagnosed by radiography, laboratory serologies (e.g., complement fixation, immunodiffusion) and/or culture. Subjects were 23-64 years of age; 28% women; 70% Caucasian, 11% Hispanic, 2% Asian, 2% Native American and 4% who did not specify race or ethnicity. Of the 51 subjects with valid skin test results, 50 subjects [98.0%; 2-sided 95% CI (89.6%, 100%)] had a mean induration of ≥ 5 mm at the Spherusol® injection site. Among subjects with valid skin test results the average size of induration at the Spherusol® injection site was 17 mm (range 5 mm-39 mm).

The receipt of concurrent or previous antifungal therapy did not appear to interfere with or accentuate the induration response to Spherusol®.

14.2 Induration Response in Subjects Without a History of Pulmonary Coccidioidomycosis or Known Exposure to C. immitis.

A single site, double-blind study conducted in a non-endemic area for C. immitis (Spokane, WA) enrolled 60 adult subjects (18-56 years of age) with no known exposure to C. immitis by travel to or residency in an endemic area. Subjects had negative serologies to C. immitis by complement fixation, immunodiffusion and/or ELISA. Subjects enrolled in the study were 65% women; 96% Caucasian, 2% Hispanic and 2% Native American. At the 48 hour (± 4 hours) assessment, a total of 55 subjects had valid skin test results (5 subjects had negative skin test results to all reagents and were considered un-interpretable). One subject (1/55) had a 5 mm mean induration response to Spherusol® and 54 subjects with demonstrated negative responses (< 5mm mean induration) to Spherusol®. Fifty-four of the 55 subjects with valid skin test responses [98.2%; 2-sided 95% CI (90.3%, > 99.9%)] demonstrated a negative induration response to Spherusol®. When the five subjects who had un-interpretable responses were analyzed as if these responses represented positive reactions to Spherusol®, 54 of 60 subjects 90.0% (CI 79.5%, 96.2%) demonstrated a negative induration response.

14.3 Induration Response in Subjects With a History of Pulmonary Histoplasmosis

A single site, double-blind study conducted in a non-endemic area for C. immitis, but endemic for H. capsulatum (Blair, NE) enrolled 12 adult subjects (33 to 60 years of age) with no known exposure to C. immitis by travel to or residency in an endemic area. All subjects had a history of pulmonary Histoplasmosis. Subjects had negative serologies to C. immitis by complement fixation, immunodiffusion and/or ELISA. Subjects were 42% women and 100% Caucasian. At the 48 hour (± 4 hours) assessment, all 12 subjects reacted to at least one of the positive controls with ≥ 5mm mean induration and demonstrated negative (< 5mm) induration responses to thimerosal and saline controls. No positive induration responses to Spherusol® were observed [1-sided 97.5% CI; (0%, 26.5%)] among subjects who had a previous history of disease caused by H. capsulatum and no history of travel to areas endemic for C. immitis. These findings support the lack of cross-reaction between the cellular immune responses induced by the two fungal species.

15 REFERENCES

1. Edwards, PQ and Palmer CE. Prevalence of sensitivity to coccodioidin, with special reference to specific and nonspecific reactions to coccidioidin. Dis Chest. 31:35. 35-60, 1957.
2. Emmons, C.W., Binford, C. H., Ulz, J.P. Kwon-Chung, K.J. Medical Mycology, Leanne Febiger, Philadelphia, Chapter 17, 230, 1977.
3. Emmons CW and Olson BJ. Studies of the role of fungi in pulmonary disease. I. Cross-reactions with histoplasmin. Pub Health Rep. 60(47):1383, 1945.
4. Levine HB, Restrepon A, Eyck DR, and Stevens DA. Spherulin and coccidioidin: cross-reactions in dermal sensitivity to histoplasmin and paracoccidioidin. Am J Epidemiol. 101(6):512, 1975.
5. Zweiman, B. Cell-mediated immunity in health and disease. Allergy Principles and Practices, Mosby, Saint Louis, Chapter 50: 696, 1998.

16 HOW SUPPLIED/STORAGE AND HANDLING

Spherusol® is available in 1 mL multidose vial.

NDC# 59584-140-01: multi-dose vial.

Store refrigerated at 2° to 8°C (35° to 46°F). Do not freeze. Discard if frozen.

Do not use after expiration date.

17 PATIENT COUNSELING INFORMATION

Patients should be:

- Informed of the potential benefits and risks of skin testing with Spherusol®.
- Instructed to report any adverse events to their healthcare provider.

PACKAGE LABEL - PRINCIPAL DISPLAY PANEL - 1 mL Vial

NDC 59584-140-01

Coccidioides immitis Spherule-Derived Skin Test Antigen

Spherusol ®

Vol:1mL (10 Tests)

Dose:0.1mL Intradermally

See Package Insert

Store: 2-8°C Rx only

Preservative: 0.4% Phenol

Mfd for Nielsen BioSciences, Inc.

San Diego, CA. 92121

Lot: 000000 (to be inserted vertically)

Exp: (to be inserted vertically)

PACKAGE LABEL - PRINCIPAL DISPLAY PANEL - 1 mL Carton

Dose: 0.1 mL intradermally. See circular. (1st panel)

Contents: 1 mL multidose vial (10 tests)

Ingredients: Coccidioides immitis spherule-derived antigen, sodium chloride, sodium borate and phenol (preservative) in Water for Injection, USP.

Rx only.
Rev. 07/19

Coccidioides immitis Spherule-Derived Skin Test Antigen (panel 2)

Spherusol ®

Skin Test Strength 1.27 mcg/0.1 mL

For use in assessing delayed-type hypersensitivity to Coccidioides immitis

Nielsen BioSciences, Inc, U.S. License 1903
Mfd. by:Allermed Laboratories, Inc. U.S. License 0467
San Diego CA 92121

Potency: Measured by delayed-type intradermal skin tests in guinea pigs. (panel 3)

Storage: Store at 2 - 8°C (36 - 46°F). Do not freeze.

No U.S. Standard of Potency.

2D GS1 serialized barcode (on end flap)

GTIN (end flap)

SN (end flap)

EXP (end flap)

Lot (end flap)